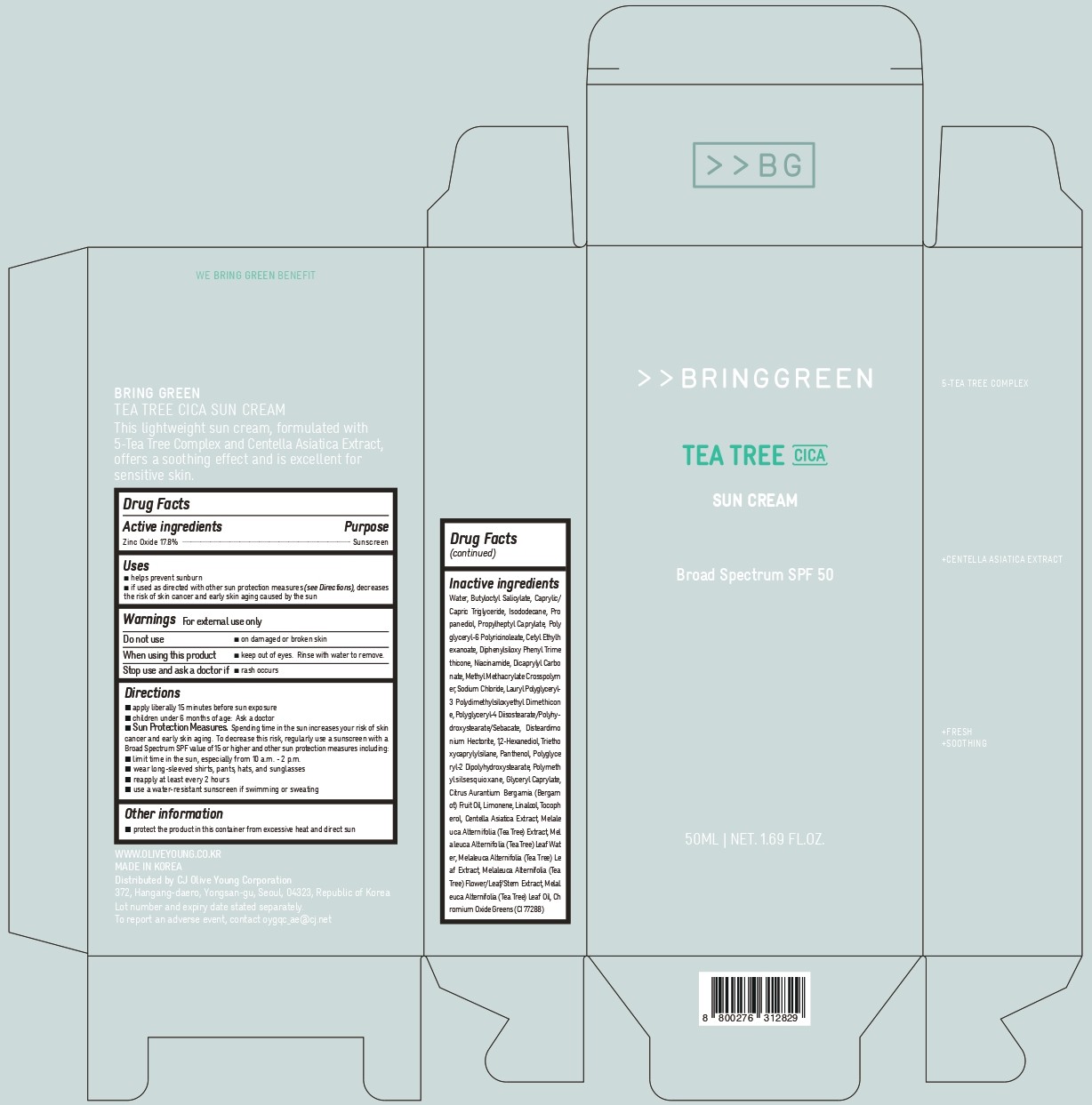 DRUG LABEL: BRING GREEN TEA TREE CICA SUNCREAM
NDC: 81540-102 | Form: CREAM
Manufacturer: CJ Olive Young Corporation
Category: otc | Type: HUMAN OTC DRUG LABEL
Date: 20251117

ACTIVE INGREDIENTS: ZINC OXIDE 8.94375 g/50 mL
INACTIVE INGREDIENTS: DISTEARDIMONIUM HECTORITE; 1,2-HEXANEDIOL; PANTHENOL; POLYGLYCERYL-2 DIPOLYHYDROXYSTEARATE; GLYCERYL CAPRYLATE; MELALEUCA ALTERNIFOLIA (TEA TREE) LEAF; MELALEUCA ALTERNIFOLIA FLOWERING TOP; PROPANEDIOL; POLYGLYCERYL-6 POLYRICINOLEATE; POLYMETHYLSILSESQUIOXANE (4.5 MICRONS); CAPRYLIC/CAPRIC TRIGLYCERIDE; CITRUS AURANTIUM BERGAMIA (BERGAMOT) FRUIT OIL; CENTELLA ASIATICA TRITERPENOIDS; TOCOPHEROL; SODIUM CHLORIDE; MELALEUCA ALTERNIFOLIA (TEA TREE) LEAF OIL; TRIETHOXYCAPRYLYLSILANE; PROPYLHEPTYL CAPRYLATE; CHROMIUM OXIDE GREENS; LAURYL POLYGLYCERYL-3 POLYDIMETHYLSILOXYETHYL DIMETHICONE (4000 MPA.S); CETYL ETHYLHEXANOATE; WATER; DICAPRYLYL CARBONATE; METHYL METHACRYLATE/GLYCOL DIMETHACRYLATE CROSSPOLYMER; BUTYLOCTYL SALICYLATE; ISODODECANE; DIPHENYLSILOXY PHENYL TRIMETHICONE; NIACINAMIDE; POLYGLYCERYL-4 DIISOSTEARATE/POLYHYDROXYSTEARATE/SEBACATE

81540-102 BRING GREEN TEA TREE CICA SUNCREAM

ACTIVE INGREDIENT

Zinc Oxide 17.8%

PURPOSE

Sunscreen

Uses

■ helps prevent sunburn

■ If used as directed with other sun protection measures (see Directions), decreases the risk of skin cancer and early skin aging caused by the sun

Warnings

For external use only

Do not use ■ on damaged or broken skin

When using this product ■ keep out of eyes. Rinse with water to remove

Stop use and ask a doctor if ■ rash occurs

■ keep out of reach of children

DOSAGE AND ADMINISTRATION

■ apply liberally 15 minutes before sun exposure ■ children under 6 months of age: Ask a doctor ■ Sun Protection Measures. Spending time in the sun increases your risk of skin cancer and early skin aging. To decrease this risk, regularly use a sunscreen with a Broad Spectrum SPF value of 15 or higher and other sun protection measures including: ■ limit time in the sun, especially from 10 a.m. - 2 p.m. ■ wear long-sleeved shirts, pants, hats, and sunglasses reapply at least every 2 hours ■ use a water-resistant sunscreen if swimming or sweating

OTHER SAFETY INFORMATION

■ protect the product in this container from excessive heat and direct sun

INACTIVE INGREDIENT

Water, Butyloctyl Salicylate, Caprylic/ Capric Triglyceride, Isododecane, Propanediol, Propylheptyl Caprylate, Polyglyceryl-6 Polyricinoleate, Cetyl Ethylhexanoate, Diphenylsiloxy Phenyl Trimethicone, Niacinamide, Dicaprylyl Carbonate, Methyl Methacrylate Crosspolymer, Sodium Chloride, Lauryl Polyglyceryl- 3 Polydimethylsiloxyethyl Dimethicon e, Polyglyceryl-4 Diisostearate/Polyhy- droxystearate/Sebacate, Disteardimonium Hectorite, 1,2-Hexanediol, Triethoxycaprylylsilane, Panthenol, Polyglyceryl-2 Dipolyhydroxystearate, Polymethylsilsesquioxane, Glyceryl Caprylate, Citrus Aurantium Bergamia (Bergam ot) Fruit Oil, Limonene, Linalool, Tocopherol, Centella Asiatica Extract, Melaleuca Alternifolia (Tea Tree) Extract, Mel aleuca Alternifolia (Tea Tree) Leaf Water, Melaleuca Alternifolia (Tea Tree) Le af Extract, Melaleuca Alternifolia (Tea Tree) Flower/Leaf/Stem Extract, Melaleuca Alternifolia (Tea Tree) Leaf Oil, Chromium Oxide Greens (CI 77288)